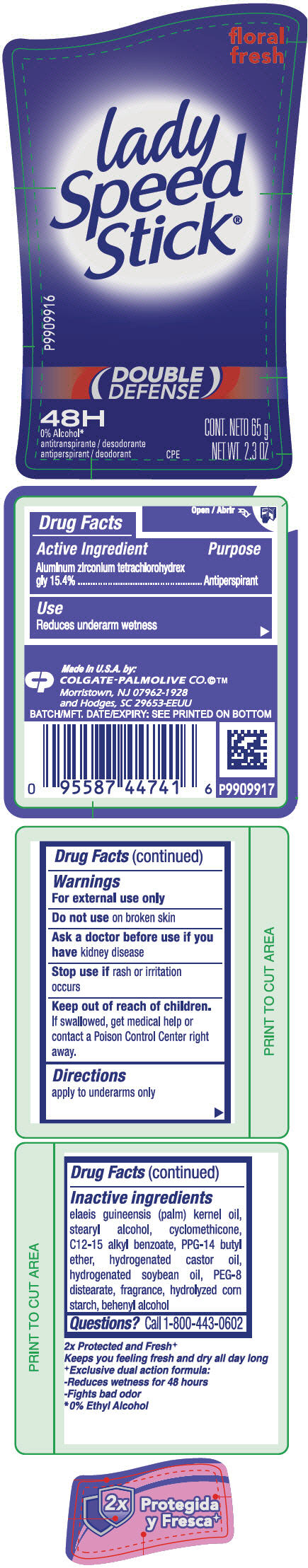 DRUG LABEL: Lady Speed Stick Double Defense Floral Fresh - antiperspirant/deodorant
NDC: 35000-397 | Form: STICK
Manufacturer: COLGATE PALMOLIVE COMPANY
Category: otc | Type: HUMAN OTC DRUG LABEL
Date: 20191216

ACTIVE INGREDIENTS: ALUMINUM ZIRCONIUM TETRACHLOROHYDREX GLY 154 mg/1 g
INACTIVE INGREDIENTS: PALM KERNEL OIL; STEARYL ALCOHOL; CYCLOMETHICONE; ALKYL (C12-15) BENZOATE; PPG-14 BUTYL ETHER; HYDROGENATED CASTOR OIL; HYDROGENATED SOYBEAN OIL; PEG-8 DISTEARATE; DOCOSANOL

Lady Speed Stick® Double Defense Floral Fresh - antiperspirant/deodorant (2.3 oz)

Drug Facts

Active Ingredient

Aluminum zirconium tetrachlorohydrex gly 15.4%

Purpose

Antiperspirant

Use

Reduces underarm wetness

Warnings

For external use only

Do not use on broken skin

Ask a doctor before use if you have kidney disease

Stop use if rash or irritation occurs

Keep out of reach of children. If swallowed, get medical help or contact a Poison Control Center right away.

Directions

apply to underarms only

Inactive ingredients

elaeis guineensis (palm) kernel oil, stearyl alcohol, cyclomethicone, C12-15 alkyl benzoate, PPG-14 butyl ether, hydrogenated castor oil, hydrogenated soybean oil, PEG-8 distearate, fragrance, hydrolyzed corn starch, behenyl alcohol

Questions?

Call 1-800-443-0602

PRINCIPAL DISPLAY PANEL - 65 g Container Label

floral
fresh

lady
Speed
Stick®

P9909916

(DOUBLE
DEFENSE)

48H

0% Alcohol*
antiperspirant / deodorant

CPE

NET WT 2.3 OZ